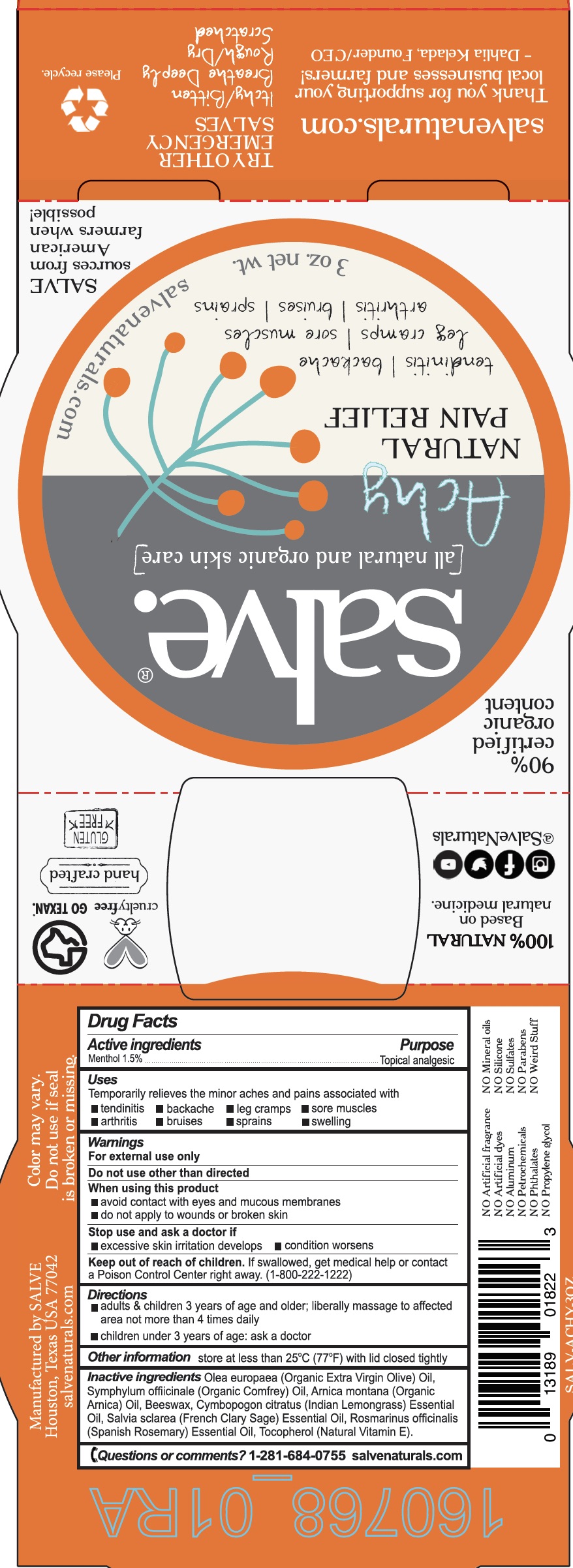 DRUG LABEL: Achy
NDC: 71157-0017 | Form: CREAM
Manufacturer: Kelada Creative Group LLC DBA SALVE
Category: otc | Type: HUMAN OTC DRUG LABEL
Date: 20161215

ACTIVE INGREDIENTS: MENTHOL 28 g/90 mL
INACTIVE INGREDIENTS: OLIVE OIL; ARNICA MONTANA FLOWER; COMFREY LEAF; WEST INDIAN LEMONGRASS OIL; ROSEMARY OIL; WHITE WAX; CLARY SAGE OIL; .ALPHA.-TOCOPHEROL

Achy external analgesic

ACTIVE INGREDIENT

Menthol 1.5%

PURPOSE

Temporarily relieves the minor aches and pains associated with tendonitis, backache, leg cramps, sore muscles, arthritis, bruises, sprains, and swelling.

Warnings

For external use only.

Do not use other than directed

When using this product

- avoid contact with eyes and mucous membranes
- do not apply tp wounds or broken skin

Stop use and ask a doctor if

- excessive skin irritation develops
- condition worsens

DOSAGE AND ADMINISTRATION

Adults and children 3 years of age and older liberally massage to affected are not more than 4 times daily

Children under 3 years of age ask a doctor before using

INACTIVE INGREDIENT

Organic extra virgin olive oil, organic comfrey oil, organic arnica oil, beeswax, Indian lemongrass essenttial oil, French clary sage essential oil, Spanish rosemary essential oil, and Natural Vitamin E

Keep out of reach of children. If swallowed get medical help or contact Poison Control Center right away (1-800-222-1222

INDICATIONS AND USAGE

Temporarily relieves the minor aches and pains associated with tendonitis, backache, leg cramps, sore muscles, arthritis, bruises, sprains, and swelling.